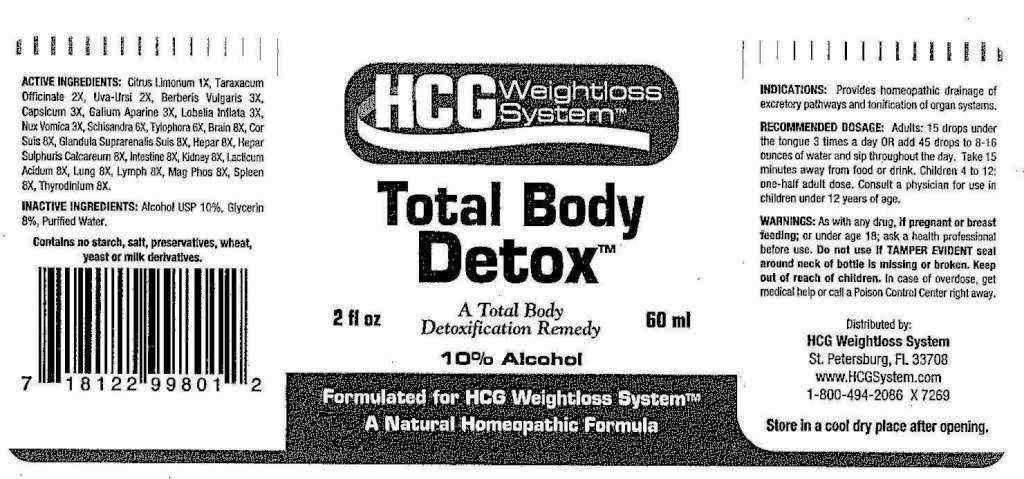 DRUG LABEL: Total Body Detox
NDC: 57520-0140 | Form: LIQUID
Manufacturer: Apotheca Company
Category: homeopathic | Type: HUMAN OTC DRUG LABEL
Date: 20110502

ACTIVE INGREDIENTS: LEMON JUICE 1 [hp_X]/1 mL; TARAXACUM OFFICINALE 2 [hp_X]/1 mL; ARCTOSTAPHYLOS UVA-URSI LEAF 2 [hp_X]/1 mL; BERBERIS VULGARIS FRUIT 3 [hp_X]/1 mL; CAPSICUM 3 [hp_X]/1 mL; GALIUM APARINE 3 [hp_X]/1 mL; LOBELIA INFLATA 3 [hp_X]/1 mL; STRYCHNOS NUX-VOMICA SEED 3 [hp_X]/1 mL; SCHISANDRA CHINENSIS FRUIT 6 [hp_X]/1 mL; SUS SCROFA ADRENAL GLAND 8 [hp_X]/1 mL; PORK INTESTINE 8 [hp_X]/1 mL; PORK LIVER 8 [hp_X]/1 mL; CALCIUM SULFIDE 8 [hp_X]/1 mL; PORK KIDNEY 8 [hp_X]/1 mL; LACTIC ACID, DL- 8 [hp_X]/1 mL; MAGNESIUM PHOSPHATE, DIBASIC TRIHYDRATE 8 [hp_X]/1 mL; SUS SCROFA SPLEEN 8 [hp_X]/1 mL; THYROID 8 [hp_X]/1 mL; PORK BRAIN 8 [hp_X]/1 mL; SUS SCROFA LUNG 8 [hp_X]/1 mL; SUS SCROFA LYMPH 8 [hp_X]/1 mL; PORK HEART 8 [hp_X]/1 mL; TYLOPHORA INDICA ROOT 6 [hp_X]/1 mL
INACTIVE INGREDIENTS: WATER; ALCOHOL; GLYCERIN

Total Body Detox

ACTIVE INGREDIENT

Active Ingredients: Citrus Limonum 1X, Taraxacum Officinale 2X, Uva-Ursi 2X, Berberis Vulgaris 3X, Capsicum Annuum 3X, Galium Aparine 3X, Lobelia Inflata 3X, Nux Vomica 3X, Schisandra 6X, Tylophora 6X, Brain 8X, Cor Suis 8X, Glandula Suprarenalis Suis 8X, Hepar Suis 8X, Hepar Sulphuris Calcareum 8X, Intestine 8X, Kidney 8X, Lacticum Acidum 8X, Lung 8X, Lymph 8X, Magnesia Phosphorica 8X, Spleen 8X, Thyroidinum 8X.

PURPOSE

Indications: Provides homeopathic drainage of excretory pathways and tonification of organ systems.

WARNINGS

WARNINGS: As with any drug, if pregnant or breast-feeding; or under age 18; ask a health professional before use.

Do not use if TAMPER EVIDENT seal around neck of bottle is broken or missing.

Keep out of reach of children. In case of overdose, get medical help or contact a Poison Control Center right away.

Store in a cool, dry place after opening.

DOSAGE AND ADMINISTRATION

Recommended Dosage: Adults: 15 drops under the tongue 3 times a day OR add 45 drops to 8-16 ounces of water and sip throughout the day. Take 15 minutes away from food or drink. Children 4 to 12: one-half adult dose. Consult a physician for use in children under 12 years of age.

Inactive Ingredients: Demineralized Water, 10% Ethanol, 8% Glycerin

Contains no starch, salt, preservatives, wheat, yeast or milk derivatives.

KEEP OUT OF REACH OF CHILDREN. In case of overdose, get medical help or contact a Poison Control Center right away.

INDICATIONS AND USAGE

INDICATIONS: Provides homeopathic drainage of excretory pathways and tonification of organ systems.

QUESTIONS

Distributed by:

HCG Weightloss System

St. Petersburg, FL 33708

www.HCGSystem.com

1-800-494-2086 X 7269

PACKAGE LABEL

HCG Weightloss System

Total Body Detox

A total Body Detoxification Remedy.

2 fl oz 60 ml

Formulated for HCG Weightloss System

A Natural Homeopathic Formula